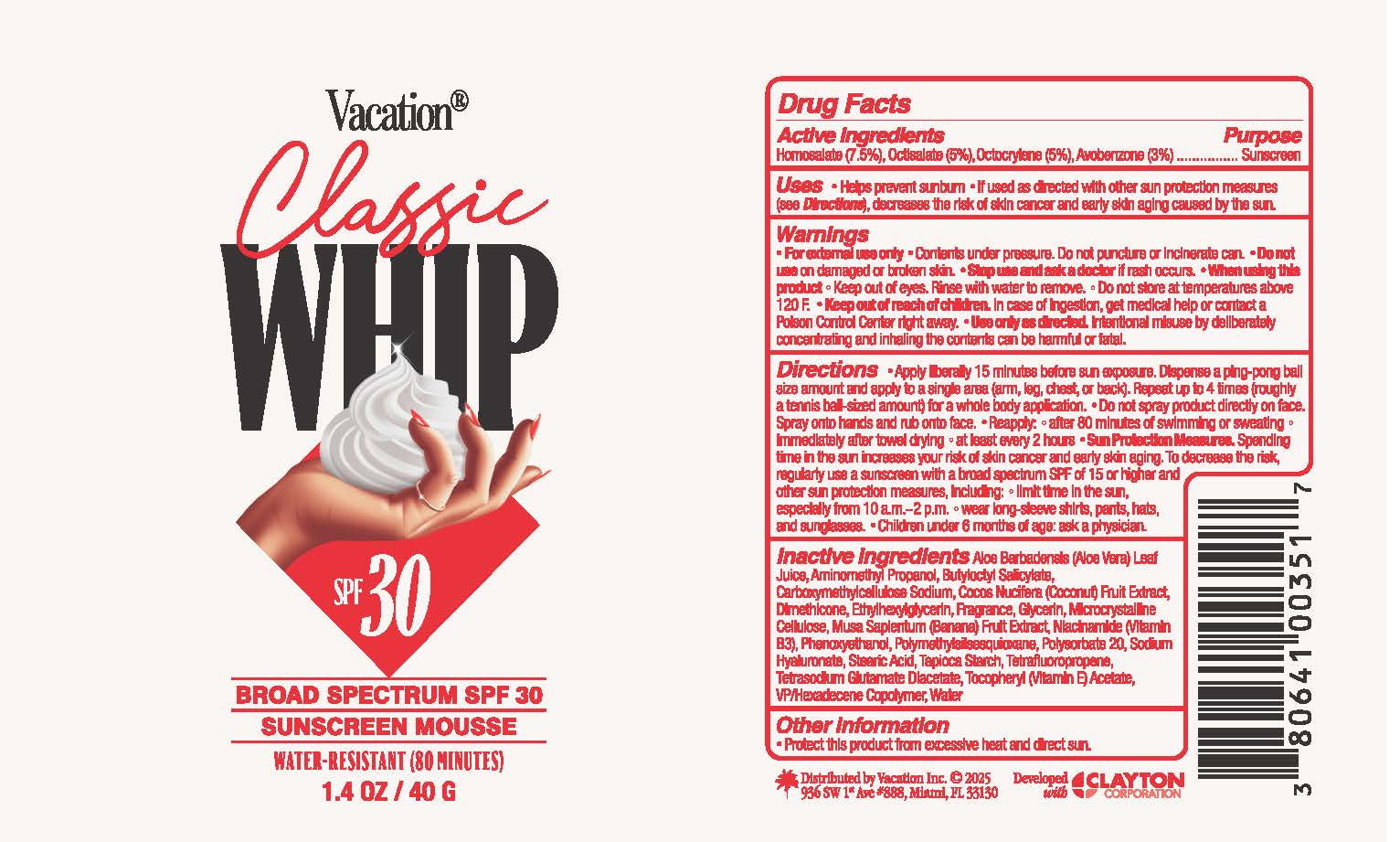 DRUG LABEL: Vacation Classic Mini Whip SPF 30
NDC: 80641-020 | Form: AEROSOL, FOAM
Manufacturer: Vacation Inc.
Category: otc | Type: HUMAN OTC DRUG LABEL
Date: 20250605

ACTIVE INGREDIENTS: AVOBENZONE 0.03 g/1 g; OCTOCRYLENE 0.05 g/1 g; HOMOSALATE 0.075 g/1 g; OCTISALATE 0.05 g/1 g
INACTIVE INGREDIENTS: WATER; COCONUT; ETHYLHEXYLGLYCERIN; CELLULOSE, MICROCRYSTALLINE; TETRASODIUM GLUTAMATE DIACETATE; DIMETHICONE; GLYCERIN; BANANA; POLYSORBATE 20; BUTYLOCTYL SALICYLATE; NIACINAMIDE; STEARIC ACID; 1,3,3,3-TETRAFLUOROPROPENE, (1E)-; VINYLPYRROLIDONE/HEXADECENE COPOLYMER; HYALURONATE SODIUM; STARCH, TAPIOCA; ALOE VERA LEAF; AMINOMETHYLPROPANOL; CARBOXYMETHYLCELLULOSE SODIUM; PHENOXYETHANOL; POLYMETHYLSILSESQUIOXANE (11 MICRONS); .ALPHA.-TOCOPHEROL ACETATE

Vacation Classic Whip SPF 30 Broad Spectrum Sunscreen Mousse

Active Ingredients

Homosalate 7.5%

Octisalate 5%

Octocrylene 5%

Avobenzone 5%

Purpose

Sunscreen

Uses

- helps prevent sunburn
- if used as directed with other sun protection measures (see Directions), decreases the risk of skin cancer and early skin aging caused by the sun

Warnings

- For external use only
- Contents under pressure. Do not puncture or incinerate can
- Do not store at temperatures above 120F
- Use only as directed. Intentional misuse by deliberately concentrating and inhaling the contents can be harmful or fatal.

Do not use

on damaged or broken skin

Stop use and ask a doctor

if rash occurs

When using this product

Keep out of eyes. Rinse with water to remove.

Keep out of reach of children

In case of ingestion, get medical help or contact a Poison Control Center right away.

Directions

- apply liberally 15 minutes before sun exposure. Dispense a ping pong ball size amount and apply to a single area (arm, leg, chest, or back). Repeat up to 4 times (roughly a tennis ball sized amount) for a whole body application
- Do not spray product directly on face. Spray onto hands and rub onto face
- Reapply:
- after 80 minutes of swimming or sweating
- immediately after towel drying
- at least every 2 hours
- Sun Protection Measures. Spending time in the sun increases your risk of skin cancer and early skin aging. To decrease the risk, regularly use a sunscreen with a broad spectrum SPF of 15 or higher and other sun protection measures including:
- Limit time in the sun, especially from 10 am - 2 pm
- wear long-sleeve shirts, pants, hats, and sunglasses
- Children under 6 months of age: ask a physician

Inactive Ingredients

Aloe Barbadensis (Aloe Vera) Leaf Juice, Aminomethyl Propanol, Butyloctyl Salicylate, Carboxymethylcellulose Sodium, Cocos Nucifera (Coconut) Fruit Extract, Dimethicone, Ethylhexylglycerin, Fragrance, Glycerin, Microcrystalline Cellulose, Musa Sapientum (Banana) Fruit Extract, Niacinamide (Vitamin B3), Phenoxyethanol, Polymethylsilsesquioxane, Polysorbate 20, Sodium Hyaluronate, Stearic Acid, Tapioca Starch, Tetrafluoropropene, Tetrasodium Glutamate Diacetate, Tocopheryl (Vitamin E) Acetate, VP/Hexadecene Copolymer, Water

Other Information

Product this product from excessive heat and direct sun